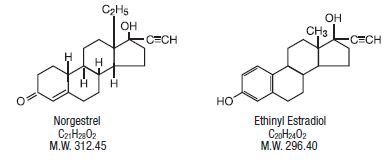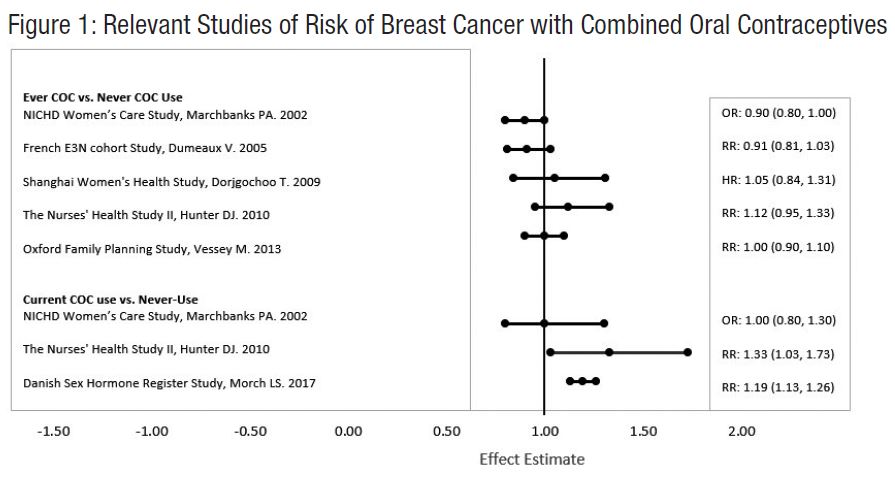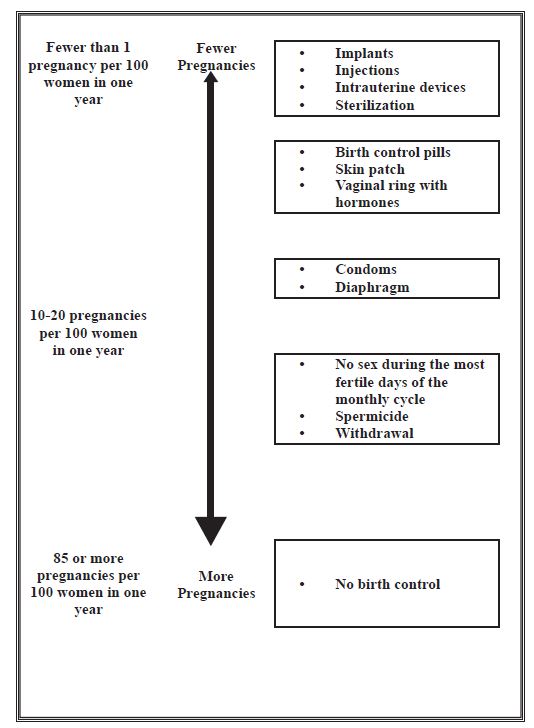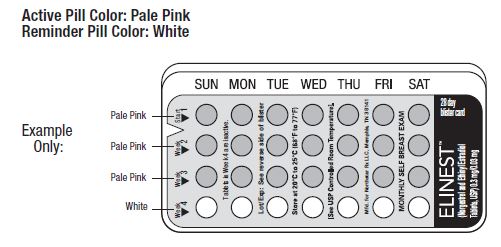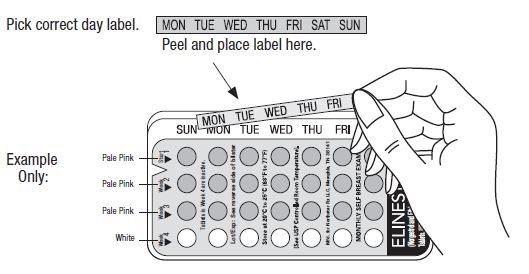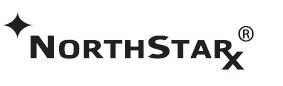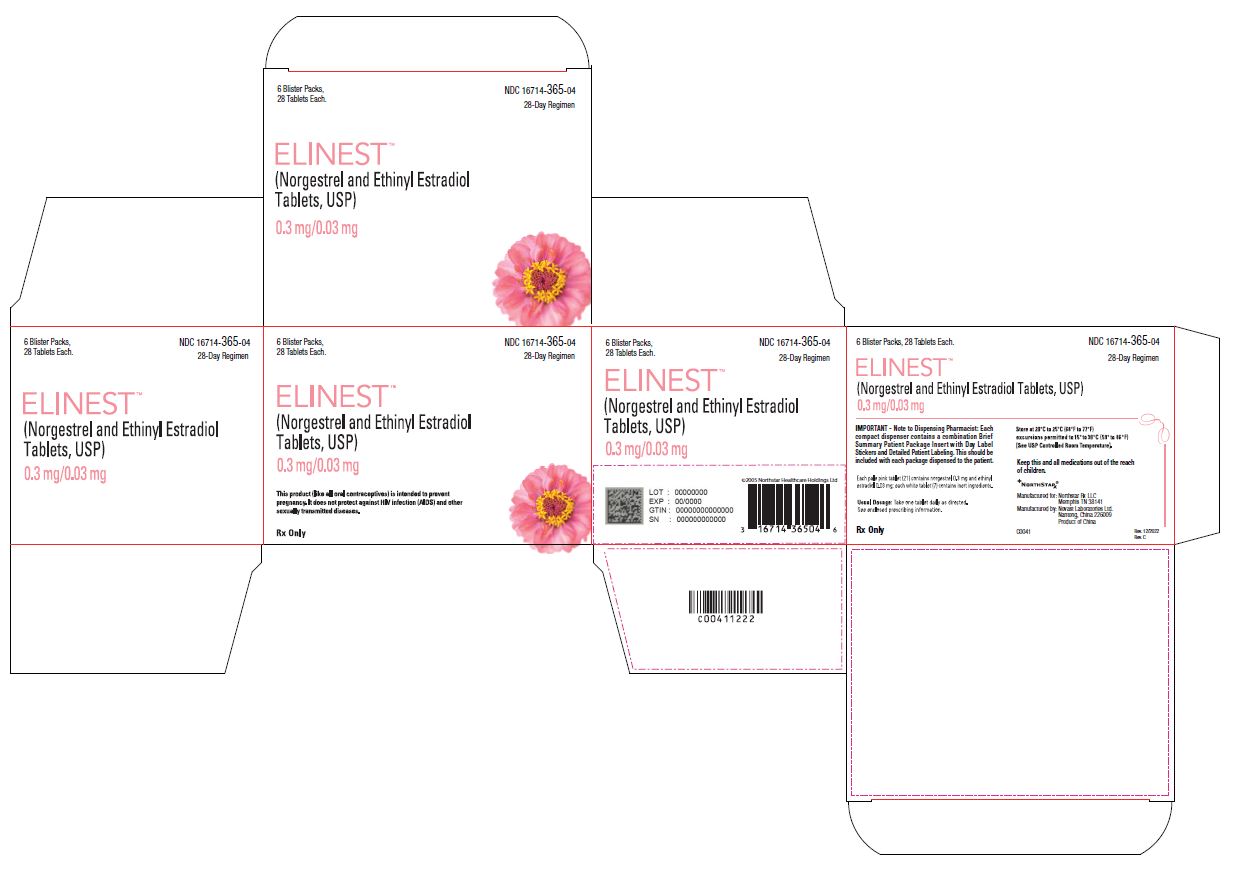 DRUG LABEL: Elinest
NDC: 16714-365 | Form: KIT | Route: ORAL
Manufacturer: Northstar Rx LLC
Category: prescription | Type: HUMAN PRESCRIPTION DRUG LABEL
Date: 20251205

ACTIVE INGREDIENTS: NORGESTREL 0.3 mg/1 1; ETHINYL ESTRADIOL 0.03 mg/1 1
INACTIVE INGREDIENTS: TITANIUM DIOXIDE; POLYETHYLENE GLYCOL 3350; TALC; POLYVINYL ALCOHOL; LECITHIN, SOYBEAN; FD&C RED NO. 40; FD&C YELLOW NO. 6; FD&C BLUE NO. 1; LACTOSE MONOHYDRATE; MAGNESIUM STEARATE; STARCH, PREGELATINIZED CORN; TITANIUM DIOXIDE; POLYDEXTROSE; HYPROMELLOSES; TRIACETIN; POLYETHYLENE GLYCOL 8000; LACTOSE MONOHYDRATE; MAGNESIUM STEARATE; STARCH, PREGELATINIZED CORN

ELINEST™
(Norgestrel and Ethinyl Estradiol Tablets, USP)
Rx only

WARNING: CIGARETTE SMOKING AND SERIOUS CARDIOVASCULAR EVENTS

Cigarette smoking increases the risk of serious cardiovascular events from combination oral contraceptive (COC) use. This risk increases with age, particularly in women over 35 years of age, and with the number of cigarettes smoked. For this reason, COCs are contraindicated in women who are over 35 years of age and smoke [see Contraindications].

DESCRIPTION

ELINESTTM is a combination oral contraceptive containing the progestational compound norgestrel and the estrogenic compound ethinyl estradiol. Norgestrel is designated as (2) (±)-13-Ethyl-17-hydroxy-18,19-dinor-17α-pregn-4-en-20-yn-3-one and ethinyl estradiol is designated as (19-nor-17α-pregna-1,3,5 (10)-trien-20-yne-3,17-diol). Each pale pink active ELINESTTM tablet contains 0.3 mg norgestrel and 0.03 mg ethinyl estradiol and the following inactive ingredients: titanium dioxide, macrogol/PEG 3350 NF, talc, polyvinyl alcohol, lecithin (soya), FD&C Red #40, FD&C Yellow #6, FD&C Blue #1, lactose monohydrate, magnesium stearate and pregelatinized starch.
Each white placebo tablet contains only the following inert ingredients: titanium dioxide, polydextrose, hypromellose, triacetin, macrogol/polyethylene glycol 8000, lactose monohydrate, magnesium stearate and pregelatinized corn starch.
Each pill pack contains 21 pale pink active tablets and 7 white inert tablets.

CLINICAL PHARMACOLOGY

Mechanism of Action

Combined oral contraceptives (COCs) prevent pregnancy primarily by suppressing ovulation.

INDICATIONS AND USAGE

ELINESTTM is indicated for use by females of reproductive potential to prevent pregnancy.

In a study of 1,287 women with a total of 11,085 cycles or 852.7 women-years of usage, the pregnancy rate in women age 15 to 40 years was approximately 1 pregnancy per 100 women-years of use.

CONTRAINDICATIONS

ELINESTTM is contraindicated in females who are known to have or develop the following conditions:

- A high risk of arterial or venous thrombotic diseases. Examples include women who are known to:

ºSmoke, if over age 35

ºHave deep-vein thrombosis or pulmonary embolism, now or in the past

ºHave inherited or acquired coagulopathies

ºHave cerebrovascular disease

ºHave coronary artery disease

ºHave thrombogenic valvular or thrombogenic rhythm diseases of the heart (for example, subacute bacterial endocarditis with valvular disease or atrial fibrillation)

ºHave uncontrolled hypertension

ºHave diabetes mellitus with vascular disease

ºHeadaches with focal neurological symptoms or migraine headaches with aura

ºWomen over age 35 with any migraine headaches

- Liver tumors, benign or malignant, or liver disease
- Undiagnosed abnormal uterine bleeding
- Pregnancy, because there is no reason to use COCs during pregnancy
- Current diagnosis or history of breast cancer, which may be hormone sensitive
- Hypersensitivity to any of the components of ELINESTTM

Women who are receiving Hepatitis C drug combinations containing ombitasvir/paritaprevir/ritonavir, with or without dasabuvir, due to the potential for ALT elevations (see Warnings, Risk of liver enzyme elevations with concomitant hepatitis c treatment).

WARNINGS

1. Thromboembolic Disorders and Other Vascular Problems

- Stop ELINESTTM if an arterial thrombotic event or venous thromboembolic (VTE) event occurs.
- Stop ELINESTTM if there is unexplained loss of vision, proptosis, diplopia, papilledema, or retinal vascular lesions. Evaluate for retinal vein thrombosis immediately.
- If feasible, stop ELINESTTM at least 4 weeks before and through 2 weeks after major surgery or other surgeries known to have an elevated risk of VTE as well as during and following prolonged immobilization.
- Start ELINESTTM no earlier than 4 weeks after delivery, in women who are not breastfeeding. The risk of postpartum VTE decreases after the third postpartum week, whereas the risk of ovulation increases after the third postpartum week.
- The use of COCs increases the risk of VTE. However, pregnancy increases the risk of VTE as much or more than the use of COCs. The risk of VTE in women using COCs is 3 to 9 cases per 10,000 woman-years. The risk of VTE is highest during the first year of use of COCs and when restarting hormonal contraception after a break of 4 weeks or longer. The risk of thromboembolic disease due to COCs gradually disappears after use is discontinued.
- Use of COCs also increases the risk of arterial thromboses such as strokes and myocardial infarctions, especially in women with other risk factors for these events. COCs have been shown to increase both the relative and attributable risks of cerebrovascular events (thrombotic and hemorrhagic strokes). This risk increases with age, particularly in women over 35 years of age who smoke.
- Use COCs with caution in women with cardiovascular disease risk factors.

2. Liver Disease

Impaired Liver Function

Do not use ELINESTTM in women with liver disease, such as acute viral hepatitis or severe (decompensated) cirrhosis of the liver [see Contraindications]. Acute or chronic disturbances of liver function may necessitate the discontinuation of COC use until markers of liver function return to normal and COC causation has been excluded. Discontinue ELINESTTM if jaundice develops.

Liver Tumors

ELINESTTM is contraindicated in women with benign and malignant liver tumors [see Contraindications]. Hepatic adenomas are associated with COC use. An estimate of the attributable risk is 3.3 cases/100,000 users. Rupture of hepatic adenomas may cause death through intra-abdominal hemorrhage.

Studies have shown an increased risk of developing hepatocellular carcinoma in long-term (>8 years) COC users. However the risk of liver cancers in COC users approaches less than one case per million users.

Risk Of Liver Enzyme Elevations With Concomitant Hepatitis C Treatment

During clinical trials with the Hepatitis C combination drug regimen that contains ombitasvir/paritaprevir/ritonavir, with or without dasabuvir, ALT elevations greater than 5 times the upper limit of normal (ULN), including some cases greater than 20 times the ULN, were significantly more frequent in women using ethinyl estradiol-containing medications such as COCs. Discontinue ELINESTTM prior to starting therapy with the combination drug regimen ombitasvir/paritaprevir/ritonavir, with or without dasabuvir [see Contraindications]. ELINESTTM can be restarted approximately 2 weeks following completion of treatment with the combination drug regimen.

3. High Blood Pressure

ELINESTTM is contraindicated in women with uncontrolled hypertension or hypertension with vascular disease [see Contraindications]. For women with well-controlled hypertension, monitor blood pressure and stop ELINESTTM if blood pressure rises significantly.

An increase in blood pressure has been reported in women taking COCs, and this increase is more likely in older women with extended duration of use. The incidence of hypertension increases with increasing quantities of progestin.

4. Gallbladder Disease

Studies suggest a small increased relative risk of developing gallbladder disease among COC users. Use of COCs may worsen existing gallbladder disease. A past history of COC-related cholestasis predicts an increased risk with subsequent COC use. Women with a history of pregnancy-related cholestasis may be at an increased risk for COC related cholestasis.

5. Carbohydrate and Lipid Metabolic Effects

Carefully monitor prediabetic and diabetic women who take ELINESTTM. COCs may decrease glucose tolerance.

Consider alternative contraception for women with uncontrolled dyslipidemia. A small proportion of women will have adverse lipid changes while on COCs.

Women with hypertriglyceridemia, or a family history thereof, may be at an increased risk of pancreatitis when using COCs.

6. Headache

If a woman taking ELINESTTM develops new headaches that are recurrent, persistent, or severe, evaluate the cause and discontinue ELINESTTM if indicated.

Consider discontinuation of ELINESTTM in the case of increased frequency or severity of migraine during COC use (which may be prodromal of a cerebrovascular event).

7. Bleeding Irregularities and Amenorrhea

Unscheduled Bleeding and Spotting

Unscheduled (breakthrough or intracyclic) bleeding and spotting sometimes occur in patients on COCs, especially during the first three months of use. If bleeding persists or occurs after previously regular cycles, check for causes such as pregnancy or malignancy. If pathology and pregnancy are excluded, bleeding irregularities may resolve over time or with a change to a different contraceptive product.

In 1,287 patients (pooled data from a number of studies), unscheduled bleeding was recorded in 15% of first cycles and by Cycle 12 was 5%. In total, 23% of subjects reported spotting, 20% reported unscheduled bleeding, and 2% reported change in menstrual flow at some point in the studies.

In the studies, 1.2% discontinued use of the product due to breakthrough bleeding and 1% discontinued due to spotting.

Amenorrhea and Oligomenorrhea

Women who use ELINESTTM may experience amenorrhea. A total of 9% of subjects in the studies reported amenorrhea in one or more cycles.

Some women may experience amenorrhea or oligomenorrhea after discontinuation of COCs, especially when such a condition was pre-existent.

If scheduled (withdrawal) bleeding does not occur, consider the possibility of pregnancy. If the patient has not adhered to the prescribed dosing schedule (missed one or more active tablets or started taking them on a day later than she should have), consider the possibility of pregnancy at the time of the first missed period and take appropriate diagnostic measures. If the patient has adhered to the prescribed regimen and misses two consecutive periods, rule out pregnancy.

8. Depression

Carefully observe women with a history of depression and discontinue ELINESTTM if depression recurs to a serious degree.

9. Malignant Neoplasms

Breast Cancer

ELINESTTM is contraindicated in females who currently have or have had breast cancer because breast cancer may be hormonally sensitive [see Contraindications].

Epidemiology studies have not found a consistent association between use of combined oral contraceptives (COCs) and breast cancer risk. Studies do not show an association between ever (current or past) use of COCs and risk of breast cancer. However, some studies report a small increase in the risk of breast cancer among current or recent users (<6 months since last use) and also among current users with longer duration of COC use [see Adverse Reactions].

Cervical Cancer

Some studies suggest that COC use has been associated with an increase in the risk of cervical cancer or intraepithelial neoplasia. However, there continues to be controversy about the extent to which such findings may be due to differences in sexual behavior and other factors.

PRECAUTIONS

1. Effect on Binding Globulins

The estrogen component of COCs may raise the serum concentrations of thyroxine-binding globulin, sex hormone-binding globulin, and cortisol-binding globulin. The dose of replacement thyroid hormone or cortisol therapy may need to be increased.

2. Hereditary Angioedema

In females with hereditary angioedema, exogenous estrogens may induce or exacerbate symptoms of angioedema.

3. Chloasma

Chloasma may occasionally occur, especially in women with a history of chloasma gravidarum. Women with a tendency to chloasma should avoid exposure to the sun or ultraviolet radiation while taking ELINESTTM.

4. Drug Interactions

Consult the labeling of all concurrently-used drugs to obtain further information about interactions with hormonal contraceptives or the potential for enzyme alterations.

Concomitant Use with HCV Combination Therapy – Liver Enzyme Elevation:

Do not co-administer ELINESTTM with HCV drug combinations containing ombitasvir/ paritaprevir/ritonavir, with or without dasabuvir, due to potential for ALT elevations (see Warnings, Risk of liver enzyme elevations with concomitant hepatitis c treatment).

Effects of Other Drugs on Combined Oral Contraceptives

Substances decreasing the plasma concentrations of COCs and potentially diminishing the efficacy of COCs: Drugs or herbal products that induce certain enzymes, including cytochrome P450 3A4 (CYP3A4), may decrease the plasma concentrations of COCs and potentially diminish the effectiveness of COCs or increase breakthrough bleeding. Some drugs or herbal products that may decrease the effectiveness of hormonal contraceptives include phenytoin, barbiturates, carbamazepine, bosentan, felbamate, griseofulvin, oxcarbazepine, rifampicin, topiramate rifabutin, rufinamide, aprepitant, and products containing St. John’s wort. Interactions between hormonal contraceptives and other drugs may lead to breakthrough bleeding and/or contraceptive failure. Counsel women to use an alternative method of contraception or a back-up method when enzyme inducers are used with COCs, and to continue back-up contraception for 28 days after discontinuing the enzyme inducer to ensure contraceptive reliability.

Colesevelam: Colesevelam, a bile acid sequestrant, given together with a COC, has been shown to significantly decrease the AUC of EE. The drug interaction between the contraceptive and colesevelam was decreased when the two drug products were given 4 hours apart.

Substances increasing the plasma concentrations of COCs: Co-administration of atorvastatin or rosuvastatin and certain COCs containing EE increase AUC values for EE by approximately 20 to 25%. Ascorbic acid and acetaminophen may increase plasma EE concentrations, possibly by inhibition of conjugation. Concomitant administration of CYP3A4 inhibitors such as itraconazole, fluconazole, grapefruit juice or ketoconazole may increase plasma hormone concentrations.

Human immunodeficiency virus (HIV)/ Hepatitis C virus (HCV) protease inhibitors and non-nucleoside reverse transcriptase inhibitors: Significant changes (increase or decrease) in the plasma concentrations of the estrogen and/or progestin have been noted when COCs are coadministered with some HIV protease inhibitors (decrease [e.g., nelfinavir, ritonavir, darunavir/ritonavir, (fos)amprenavir/ritonavir, lopinavir/ritonavir, and tipranavir/ritonavir], or increase [e.g., indinavir and atazanavir/ritonavir] HCV protease inhibitors (decrease [e.g., nevirapine] or increase [e.g., etravirine]).

Effects of Combined Oral Contraceptives on Other Drugs

COCs containing EE may inhibit the metabolism of other drugs (e.g., cyclosporine, prednisolone, theophylline, tizanidine, and voriconazole) and increase their plasma concentrations. COCs have been shown to decrease plasma concentrations of acetaminophen, clofibric acid, morphine, salicylic acid, temazepam and lamotrigine. Significant decrease in the plasma concentration of lamotrigine has been shown, likely due to induction of lamotrigine glucuronidation. This may reduce seizure control; therefore, dosage adjustments of lamotrigine may be necessary.

Women on thyroid hormone replacement therapy may need increased doses of thyroid hormone because serum concentration of thyroid-binding globulin increases with use of COCs.

5. Interference with Laboratory Tests

The use of contraceptive steroids may influence the results of certain laboratory tests, such as coagulation factors, lipids, glucose tolerance, and binding proteins.

6. Carcinogenesis

See WARNINGS Sections 2 and PRECAUTIONS Section 1.

7. Pregnancy

There is little or no increased risk of birth defects in women who inadvertently use COCs during early pregnancy. Epidemiologic studies and meta-analyses have not found an increased risk of genital or nongenital birth defects (including cardiac anomalies and limb reduction defects) following exposure to low dose COCs prior to conception or during early pregnancy.

Discontinue ELINESTTM use if pregnancy is confirmed.

Do not administer COCs to induce withdrawal bleeding as a test for pregnancy. Do not use COCs during pregnancy to treat threatened or habitual abortion.

8. Nursing Mothers

Advise the nursing mother to use other forms of contraception, when possible, until she has weaned her child. COCs can reduce milk production in breastfeeding mothers. This is less likely to occur once breastfeeding is well-established; however, it can occur at any time in some women. Small amounts of oral contraceptive steroids and/or metabolites are present in breast milk.

9. Pediatric Use

Safety and efficacy of norgestrel and ethinyl estradiol tablets have been established in women of reproductive age. Efficacy is expected to be the same for post-pubertal adolescents under the age of 16 and for users 16 years and older. Use of ELINESTTM before menarche is not indicated.

10. Geriatric Use

ELINESTTM has not been studied in postmenopausal women and is not indicated in this population.

11. Information for the Patient

See FDA-approved patient labeling (Patient Information and Instructions for Use). Counsel patients about the following information:

- Cigarette smoking increases the risk of serious cardiovascular events from COC use, and that women who are over 35 years old and smoke should not use COCs [see Boxed Warning].
- Increased risk of VTE compared to non-users of COCs is greatest after initially starting a COC or restarting (following a 4-week or greater pill-free interval) the same or a different COC.
- ELINESTTM does not protect against HIV infection and other sexually transmitted infections.
- ELINESTTM is not to be used during pregnancy; if pregnancy occurs during use of ELINESTTM, instruct the patient to stop further use.
- Take one tablet daily by mouth at the same time every day. Instruct patients what to do in the event tablets are missed.
- Use a back-up or alternative method of contraception when enzyme inducers are used with ELINESTTM.
- COCs may reduce breast milk production; this is less likely to occur if breastfeeding is well established.
- Women who start COCs postpartum, and who have not yet had a period, should use an additional method of contraception until they have taken an active tablet for 7 consecutive days.
- Amenorrhea may occur. Consider pregnancy in the event of amenorrhea at the time of the first missed period. Rule out pregnancy in the event of amenorrhea in two or more consecutive cycles.

ADVERSE REACTIONS

An increased risk of the following serious adverse reactions (see Warnings section for additional information) has been associated with the use of oral contraceptives:

- Serious cardiovascular events and stroke [see Boxed Warning]
- Vascular events
- Liver disease

Adverse reactions commonly reported by COC users are:

- Irregular uterine bleeding
- Nausea
- Breast tenderness
- Headache

Clinical Trials Experience

Because clinical trials are conducted under widely varying conditions, adverse reaction rates observed in the clinical trials of a drug cannot be directly compared to rates in the clinical trials of another drug and may not reflect the rates observed in clinical practice.

The safety of norgestrel and ethinyl estradiol tablets was evaluated in 1,343 healthy women of child-bearing potential who participated in 9 clinical trials and received at least one dose of norgestrel and ethinyl estradiol tablets for contraception. Subjects were exposed for a total of 11,085 cycles, with 429 women completing one year of exposure. Subjects ranged in age from 15 to 40 years. Demographics were 69% Caucasian, 28% Black, and 3% other.

Common Adverse Reactions (≥ 2% of women):

- Weight increase (11%)
- Cervical erosion (9%)
- Weight decrease (6%)
- Acne (4%)
- Dysmenorrhea (4%)
- Vaginal discharge (4%)
- Abdominal pain, cramps, and bloating (3%)
- Appetite increase (3%)
- Depression (3%)
- Nervousness (3%)
- Chloasma/melasma (2%)
- Fatigue (2%)
- Varicose veins, aggravation of (2%)

A total of 8% of subjects discontinued the trials prematurely due to an adverse reaction, most commonly due to unscheduled bleeding, spotting, headache (including migraine), nausea, acne, changes in menstrual flow, weight increase, nervousness, high blood pressure, and depression.

Postmarketing Experience

Five studies that compared breast cancer risk between ever-users (current or past use) of COCs and never-users of COCs reported no association between ever use of COCs and breast cancer risk, with effect estimates ranging from 0.90 to 1.12 (Figure 1).

Three studies compared breast cancer risk between current or recent COC users (<6 months since last use) and never users of COCs (Figure 1). One of these studies reported no association between breast cancer risk and COC use. The other two studies found an increased relative risk of 1.19 to 1.33 with current or recent use. Both of these studies found an increased risk of breast cancer with current use of longer duration, with relative risks ranging from 1.03 with less than one year of COC use to approximately 1.4 with more than 8-10 years of COC use.

RR = relative risk; OR = odds ratio; HR = hazard ratio. “ever COC” are females with current or past COC use; “never COC use” are females that never used COCs.

The following additional adverse drug reactions have been reported from worldwide postmarketing experience with norgestrel and ethinyl estradiol tablets. Because these reactions are reported voluntarily from a population of uncertain size, it is not always possible to reliably estimate their frequency or establish a causal relationship to drug exposure.

Arterial Events: Arterial thromboembolism, Myocardial infarction, Cerebral hemorrhage

Eye Disorder: Optic neuritis, which may lead to partial or complete loss of vision, Intolerance to contact lenses, Change (steepening) in corneal curvature

Gastrointestinal Disorders: Colitis, Nausea, Pancreatitis

Hepatobiliary Disorders: Gallbladder disease, Cholestatic jaundice, Budd-Chiari syndrome

Immune System Disorders: Anaphylactic/anaphylactoid reactions, including urticaria, angioedema, and severe reactions with respiratory and circulatory symptoms

Metabolism and Nutrition Disorders: Carbohydrate and lipid effects, Porphyria, exacerbation of Porphyria

Neoplasms, Benign, Malignant, and Unspecified: Carcinoma of the reproductive organs and breasts, Hepatic neoplasia (including hepatic adenomas or benign liver tumors)

Psychiatric Disorders: Mood changes

Reproductive System and Breast Disorders: Temporary infertility after discontinuation of treatment, Changes in libido, Vaginitis, including candidiasis; Breast secretion

Skin and Subcutaneous Tissue Disorders: Melasma/chloasma, which may persist; Erythema multiforme, Erythema nodosum, Hemorrhagic eruption, Hirsutism

Vascular Events: Venous thrombosis, Pulmonary embolism, Cerebral thrombosis, Mesenteric thrombosis, Retinal vascular thrombosis

OVERDOSAGE

There have been no reports of serious ill effects from overdosage of oral contraceptives, including ingestion by children. Overdosage may cause withdrawal bleeding in females and nausea.

DOSAGE AND ADMINISTRATION

To achieve maximum contraceptive effectiveness, ELINESTTM (norgestrel and ethinyl estradiol tablets) must be taken exactly as directed and at intervals not exceeding 24 hours. The dosage of ELINESTTM is one pale pink tablet daily for 21 consecutive days, followed by one white inert tablet daily for 7 consecutive days, according to prescribed schedule. It is recommended that ELINESTTM tablets be taken by mouth at the same time each day.

How to Start ELINESTTM

Consider the possibility of ovulation and conception prior to initiation of medication.

Instruct the patient to begin taking ELINESTTM on the first Sunday after the onset of menstruation. If menstruation begins on a Sunday, the first tablet (pale pink) is taken that day. The patient should take one pale pink tablet daily for 21 consecutive days followed by one white inert tablet daily for 7 consecutive days. Withdrawal bleeding will usually occur within 3 days following discontinuation of pale pink tablets and may not have finished before the next pack is started. During the first cycle, the patient should not rely on ELINESTTM for contraception until a pale pink tablet has been taken daily for 7 consecutive days and she should use a non-hormonal back-up method of birth control during those 7 days.

After the first cycle of use

The patient is to begin her next and all subsequent 28-day courses of tablets on the same day of the week (Sunday) on which she began her first course, following the same schedule: 21 days of pale pink tablets, followed by 7 days of white inert tablets. If in any cycle the patient starts tablets later than the proper day, instruct her to protect herself against pregnancy by using a non-hormonal back-up method of birth control until she has taken a pale pink tablet daily for 7 consecutive days.

Switching from another hormonal method of contraception

- When the patient is switching from a 21-day regimen of tablets, instruct her to wait 7 days after her last tablet before she starts ELINESTTM. She will probably experience withdrawal bleeding during that week. Instruct her not to let more than 7 days pass after her previous 21-day regimen before she starts ELINESTTM.
- When the patient is switching from a 28-day regimen of tablets, instruct her to start her first pack of ELINESTTM on the day after her last tablet. She should not wait any days between packs.
- The patient may switch any day from a progestin-only pill and should begin ELINESTTM the next day. If switching from an implant or injection, instruct the patient to start ELINESTTM on the day of implant removal or the day the next injection would be due. If switching from a contraceptive vaginal ring or transdermal patch instruct the patient to start ELINESTTM on the day they would have inserted the next ring or applied the next patch. If switching from an Intrauterine Device (IUD) or Intrauterine System (IUS), instruct the patient to start ELINESTTM on the day of IUD/IUS removal. If the IUD/IUS is not removed on the first day of the patient’s menstrual cycle, instruct her to use a non-hormonal back-up method of birth control for the first 7 days of tablet-taking.

Use after pregnancy, abortion, or miscarriage

- Initiate ELINESTTM no earlier than day 28 postpartum in the nonlactating mother or after a second-trimester abortion due to the increased risk for thromboembolism (see Contraindications, Warnings and Precautionsconcerning thromboembolic disease). Advise the patient to use a non-hormonal back-up method for the first 7 days of tablet-taking.
- ELINESTTM may be initiated immediately after a first-trimester abortion or miscarriage. If the patient starts ELINESTTM immediately, back-up contraception is not needed.

If spotting or breakthrough bleeding occurs

If spotting or breakthrough bleeding occurs, instruct the patient to continue on the same regimen. This type of bleeding is usually transient and without significance; however, advise the patient to consult her healthcare provider if the bleeding is persistent or prolonged.

Missed Tablets

The possibility of ovulation and pregnancy increases with each successive day that scheduled pale pink tablets are missed. If withdrawal bleeding does not occur, the possibility of pregnancy must be considered. If the patient has not adhered to the prescribed schedule (if she missed one or more tablets or started taking them on a day later than she should have), consider the probability of pregnancy at the time of the first missed period and take appropriate diagnostic measures. If the patient has adhered to the prescribed regimen and misses two consecutive periods, rule out pregnancy.

For additional patient instructions regarding missed tablets, see the WHAT TO DO IF YOU MISS PILLS section in FDA-Approved Patient Labeling below.

Advice in Case of Gastrointestinal Disturbances

In case of severe vomiting or diarrhea, absorption may not be complete and additional contraceptive measures should be taken. If vomiting or diarrhea occurs within 3 to 4 hours after taking an active tablet, handle this as a missed tablet [see FDA-Approved Patient Labeling].

HOW SUPPLIED

ELINEST™ Tablets (Norgestrel and Ethinyl Estradiol Tablets USP, 0.3 mg/0.03 mg): Each pale pink tablet is biconvex, round, with “E1” debossed on one side, and contains 0.3 mg norgestrel and 0.03 mg ethinyl estradiol. ELINEST™ blisters (NDC 16714-365-01) are packaged in cartons of one, three, and six 28-tablet dispensers. Each tablet dispenser contains 21 pale pink (active) tablets and 7 white (inert) tablets. Inert tablets are biconvex, round, with “P” debossed on one side and “N” on the other side.

ELINEST™ Tablets are available in the following:
Carton of 1 NDC 16714-365-02
Carton of 3 NDC 16714-365-03
Carton of 6 NDC 16714-365-04

Store at 20°C to 25°C (68°F to 77°F) [See USP Controlled Room Temperature].

PATIENT INFORMATION

FDA-Approved Patient Labeling

ELINESTTM [ee-lin-EST]

(norgestrel and ethinyl estradiol tablets)

What is the most important information I should know about ELINESTTM?

Do not use ELINESTTM if you smoke cigarettes and are over 35 years old. Smoking increases your risk of serious cardiovascular side effects from hormonal birth control pills, including death from heart attack, blood clots or stroke. This risk increases with age and the number of cigarettes you smoke.

What is ELINESTTM?

ELINESTTM is a birth control pill (oral contraceptive) used by women to prevent pregnancy.

How does ELINESTTM work for contraception?

Your chance of getting pregnant depends on how well you follow the directions for taking your birth control pills. The better you follow the directions, the less chance you have of getting pregnant.

Based on the results of clinical studies, about 1 out of 100 women may get pregnant during the first year they use norgestrel and ethinyl estradiol tablets.

The following chart shows the chance of getting pregnant for women who use different methods of birth control. Each box on the chart contains a list of birth control methods that are similar in effectiveness. The most effective methods are at the top of the chart. The box on the bottom of the chart shows the chance of getting pregnant for women who do not use birth control and are trying to get pregnant.

Who should not take ELINESTTM?

Do not take ELINESTTM if you:

- smoke and are over 35 years old
- had blood clots in the legs, arms, lungs, or eyes
- had a problem with your blood that makes it clot more than normal
- have certain heart valve problems or irregular heart beat that increases your risk of having blood clots
- had a stroke
- had a heart attack
- have high blood pressure that cannot be controlled by medicine
- have diabetes with kidney, eye, nerve or blood vessel damage
- have certain kinds of severe migraine headaches with aura, numbness, weakness or changes in vision, or have any migraine headaches if you are over 35 years of age
- have liver problems, including liver tumors
- have any unexplained vaginal bleeding
- are pregnant
- have or had breast cancer
- have a known allergy or hypersensitivity to any of the components of ELINESTTM (norgestrel and ethinyl estradiol tablets)

You should not take the pill if you take any Hepatitis C drug combination containing ombitasvir/paritaprevir/ritonavir, with or without dasabuvir. This may increase levels of the liver enzyme “alanine aminotransferase” (ALT) in the blood.

If any of these conditions happen while you are taking ELINESTTM, stop taking ELINESTTM right away and talk to your healthcare provider. Use non-hormonal contraception when you stop taking ELINESTTM.

What should I tell my healthcare provider before taking ELINESTTM?

Tell your healthcare provider if you:

- are pregnant or think you may be pregnant
- are depressed now or have been depressed in the past
- had yellowing of your skin or eyes (jaundice) caused by pregnancy (cholestasis of pregnancy)
- have a condition called hereditary angioedema
- are breastfeeding or plan to breastfeed. ELINESTTM may decrease the amount of breast milk you make. A small amount of the hormones in ELINESTTM may pass into your breast milk. Talk to your healthcare provider about the best birth control method for you while breastfeeding.

Tell your healthcare provider about all the medicines you take, including prescription and over-the-counter medicines, vitamins and herbal supplements.

ELINESTTM may affect the way other medicines work, and other medicines may affect how well ELINESTTM works.

Know the medicines you take. Keep a list of them to show your healthcare provider and pharmacist when you get a new medicine.

How should I take ELINESTTM?

Read the Instructions for Use at the end of this Patient Information.

What are the possible serious side effects of ELINESTTM?

- Like pregnancy, ELINESTTM may cause serious side effects, including blood clots in your lungs , heart attack, or a stroke that may lead to death.
- Some other examples of serious blood clots include blood clots in the legs or eyes.

Serious blood clots can happen especially if you smoke, are obese, or are older than 35 years of age. Serious blood clots are more likely to happen when you:

- first start taking birth control pills
- restart the same or different birth control pills after not using them for a month or more

Call your healthcare provider or go to a hospital emergency room right away if you have:

- leg pain that will not go away
- sudden severe shortness of breath
- sudden change in vision or blindness
- chest pain
- a sudden, severe headache unlike your usual headaches
- weakness or numbness in your arm or leg
- trouble speaking

Other serious side effects include:

- liver problems, including:

ºrare liver tumors

ºjaundice (cholestasis), especially if you previously had cholestasis of pregnancy. Call your healthcare provider if you have yellowing of your skin or eyes.

- high blood pressure
- gallbladder problems
- changes in the sugar and fat (cholesterol and triglycerides) levels in your blood
- new or worsening headaches including migraine headaches
- depression
- possible cancer in your breast and cervix
- swelling of your skin especially around your mouth, eyes, and in your throat (angioedema). Call your healthcare provider if you have a swollen face, lips, mouth tongue or throat, which may lead to difficulty swallowing or breathing. Your chance of having angioedema is higher is you have a history of angioedema.

What are the most common side effects of ELINESTTM?

- menstrual complaints, including unscheduled bleeding and spotting
- nausea
- headache (including migraine)
- weight increase or decrease
- cervical erosion
- acne
- menstrual cramps
- vaginal discharge
- stomach pain, discomfort, and gas
- increase in appetite
- depression
- nervousness
- dark areas on your face
- fatigue
- worsening of varicose veins

These are not all the possible side effects of ELINESTTM. For more information, ask your healthcare provider or pharmacist. You may report side effects to the FDA at 1-800-FDA-1088.

What else should I know about taking ELINESTTM?

- If you are scheduled for any lab tests, tell your healthcare provider you are taking ELINESTTM. Certain blood tests may be affected by ELINESTTM.
- ELINESTTM does not protect against HIV infection (AIDS) and other sexually transmitted infections.

How should I store ELINESTTM?

- Store ELINESTTM at room temperature between 68°F to 77°F (20°C to 25°C).
- Keep ELINESTTM and all medicines out of the reach of children.
- Store away from light.

General information about the safe and effective use of ELINESTTM:

Medicines are sometimes prescribed for purposes other than those listed in a Patient Information leaflet. Do not use ELINESTTM for a condition for which it was not prescribed. Do not give ELINESTTM to other people, even if they have the same symptoms that you have.

This Patient Information summarizes the most important information about ELINESTTM. You can ask your pharmacist or healthcare provider for information about ELINESTTM that is written for health professionals. For more information, call 1-800-206-7821.

Do birth control pills cause cancer?

It is not known if hormonal birth control pills cause breast cancer. Some studies, but not all, suggest that there could be a slight increase in the risk of breast cancer among current users with longer duration of use.

If you have breast cancer now, or have had it in the past, do not use birth control pills because some breast cancers are sensitive to hormones.

Women who use birth control pills may have a slightly higher chance of getting cervical cancer. However, this may be due to other reasons such as having more sexual partners.

What if I want to become pregnant?

You may stop taking the pill whenever you wish. Consider a visit with your healthcare provider for a pre-pregnancy checkup before you stop taking the pill.

What should I know about my period when taking ELINESTTM?

Your periods may be lighter and shorter than usual. Some women may miss a period. Irregular vaginal bleeding or spotting may happen while you are taking ELINESTTM, especially during the first few months of use. This usually is not a serious problem. It is important to continue taking your pills on a regular schedule to prevent a pregnancy.

What are the ingredients in ELINESTTM?

Active ingredients:

Each pale pink pill contains norgestrel and ethinyl estradiol.

Inactive ingredients:

Pale pink pills: titanium dioxide, macrogol/PEG 3350 NF, talc, polyvinyl alcohol, lecithin (soya), FD&C Red #40, FD&C Yellow #6, FD&C Blue #1, lactose monohydrate, magnesium stearate and pregelatinized starch.

White pills: titanium dioxide, polydextrose, hypromellose, triacetin, macrogol/polyethylene glycol 8000, lactose monohydrate, magnesium stearate and pregelatinized corn starch.

INSTRUCTIONS FOR USE

Important Information about taking ELINESTTM

- Take 1 pill every day at the same time. Take the pills in the order directed on your pill dispenser.
- Do not skip your pills, even if you do not have sex often. If you miss pills (including starting the pack late) you could get pregnant. The more pills you miss, the more likely you are to get pregnant.
- If you have trouble remembering to take ELINESTTM, talk to your healthcare provider.
- When you first start taking ELINESTTM, spotting or light bleeding in between your periods may occur. Contact your healthcare provider if this does not go away after a few months.
- You may feel sick to your stomach (nauseous), especially during the first few months of taking ELINESTTM. If you feel sick to your stomach, do not stop taking the pill. The problem will usually go away. If your nausea does not go away, call your healthcare provider.
- Missing pills can also cause spotting or light bleeding, even when you take the missed pills later. On the days you take 2 pills to make up for missed pills (see WHAT TO DO IF YOU MISS PILLS? below), you could also feel a little sick to your stomach.
- It is not uncommon to miss a period. However, if you miss a period and have not taken ELINESTTM according to directions, or miss 2 periods in a row, or feel like you may be pregnant, call your healthcare provider. If you have a positive pregnancy test, you should stop taking ELINESTTM.
- If you have vomiting or diarrhea within 3 to 4 hours of taking your pill, take another pill of the same color from your extra pill dispenser. If you do not have an extra pill dispenser, take the next pill in the dispenser you are currently using. Continue taking all your remaining pills in order. Start the first pill of your next pill dispenser the day after finishing your current pill dispenser. This will be 1 day earlier than originally scheduled. Continue on your new schedule.
- If you have vomiting or diarrhea for more than 1 day, your birth control pills may not work as well. Use an additional birth control method, like condoms or spermicide, until you check with your healthcare provider.
- Stop taking ELINESTTM at least 4 weeks before you have major surgery and do not restart after the surgery without asking your healthcare provider. Be sure to use another form of contraception (like condoms or spermicide) during this time period.

BEFORE YOU START TAKING ELINESTTM

1.DECIDE WHAT TIME OF DAY YOU WANT TO TAKE YOUR PILL.

It is important to take it at about the same time every day.

2.LOOK AT YOUR PILL PACK:
The pill pack has 21 "active" pale pink pills (with hormones) to take for 3 weeks, followed by 1 week of reminder white pills (without hormones).

3.FIND:
1) where on the pack to start taking pills, and
2) in what order to take the pills (follow the arrows)

4. BE SURE YOU HAVE READY AT ALL TIMES:

•Another kind of birth control (such as condoms or spermicide) to use as a back-up in case you miss pills•An extra, full pill pack

WHEN TO START THE FIRST PACK OF PILLS
You have a choice of which day to start taking your first pack of pills. Decide with your doctor or clinic which is the best day for you. Pick a time of day which will be easy to remember.

DAY 1 START:

1. Pick the day label strip that starts with the first day of your period. Place this day label strip over the area that has the days of the week (starting with Sunday) pre-printed on the tablet dispenser.

Note: if the first day of your period is a Sunday, you can skip step #1.

2. Take the first “active” pale pink pill of the first pack during the first 24 hours of your period.

3. You will not need to use a back-up method of birth control, since you are starting the pill at the beginning of your period.

SUNDAY START:

1.Take the first "active" pale pink pill of the first pack on the Sunday after your period starts, even if you are still bleeding. If your period begins on Sunday, start the pack that same day.

2.Use a non-hormonal method of birth control(such as condoms or spermicide) as a back-up method if you have sex anytime from the Sunday you start your first pack until the next Sunday (7 days).

WHAT TO DO DURING THE MONTH

1. Take one pill at the same time every day until the pack is empty.
Do not skip pills even if you are spotting or bleeding between monthly periods or feel sick to your stomach (nausea).
Do not skip pills even if you do not have sex very often.

2. When you finish a pack:
Start the next pack on the day after your last “reminder” pill. Do not wait any days between packs.

IF YOU SWITCH FROM ANOTHER BRAND OF COMBINATION PILLS:

If your previous brand had 21 pills: Wait 7 days to start taking ELINESTTM. You will probably have your period during that week. Ideally, be sure that no more than 7 days pass between the 21-day pack and taking the first pale pink ELINESTTM pill (“active” with hormone). If you start ELINESTTM more than 7 days after taking the last pill of your previous contraceptive, you must use a non-hormonal back-up method of birth control during the first 7 days of ELINESTTM use.

If your previous brand had 28 pills: Start taking the first pale pink ELINESTTM pill (“active” with hormone) on the day after your last reminder pill. Ideally, do not wait any days between packs. If you do skip any days between the last pill of your previous contraceptive and starting ELINESTTM, you must use a non-hormonal back-up method of birth control during the first 7 days of ELINESTTM use.

IF YOU SWITCH FROM ANOTHER TYPE OF BIRTH CONTROL METHOD:

If you were previously taking a progestin-only PILL: You may switch to ELINESTTM on any day from a progestin-only pill and should start taking the first pale pink ELINESTTM pill (“active” with hormone) the day after you take your last progestin-only pill. In addition, use a non-hormonal back-up method of birth control for the first 7 days of tablet-taking.

If you are switching from a contraceptive vaginal ring or transdermal patch: Start taking the first pale pink ELINESTTM pill (“active” with hormone) on the day that you would have inserted a new ring or applied a new patch.

If you are switching from a contraceptive implant: Start taking the first pale pink ELINESTTM pill (“active” with hormone) on the day that the implant is removed.

If you are switching from a contraceptive injection: Start taking the first pale pink ELINESTTM pill (“active” with hormone) on the day that the next contraceptive injection is due.

If you are switching from an Intrauterine device (IUD) or Intrauterine system (IUS): Start taking the first pale pink ELINESTTM pill (“active” with hormone) on the day the IUD/IUS is removed. If your IUD/IUS is removed on the first day of your period you do not need to use an additional non-hormonal back up method of birth control. If the IUD/IUS is removed on any other day, use a non-hormonal back-up method of birth control for the first 7 days of tablet-taking.

WHAT TO DO IF YOU MISS PILLS

ELINESTTM may not be as effective if you miss pale pink “active” pills, and particularly if you miss the first few or the last few pale pink “active” pills in a pack.

If you MISS 1 pale pink “active” pill:

1.Take it as soon as you remember. Take the next pill at your regular time. This means you may take 2 pills in 1 day.2.You could become pregnant if you have sex in the 7 days after you restart your pills. You MUST use a non-hormonal birth control method (such as condoms or spermicide) as a back-up for those 7 days.

If you MISS 2 pale pink “active” pills in a row in WEEK 1 OR WEEK 2 of your pack:

1.Take 2 pills on the day you remember and 2 pills the next day.2.Then take 1 pill a day until you finish the pack.3.You could become pregnant if you have sex in the 7 days after you restart your pills. You MUST use a non-hormonal birth control method (such as condoms or spermicide) as a back-up for those 7 days.

If you MISS 2 pale pink“active” pills in a row in THE 3rd WEEK:

1.Keep taking 1 pill every day until Sunday. On Sunday, throw out the rest of the pack and start a new pack of pills that same day.2.You may not have your period this month but this is expected. However, if you miss your period 2 months in a row, call your healthcare provider because you might be pregnant.3.You could become pregnant if you have sex in the 7 days after you restart your pills. You MUST use a non-hormonal birth control method (such as condoms or spermicide) as a back-up for those 7 days.

If you MISS 3 OR MORE pale pink “active” pills in a row (during the first 3 weeks):

1.Keep taking 1 pill every day until Sunday. On Sunday, throw out the rest of the pack and start a new pack of pills that same day.2.You may not have your period this month but this is expected. However, if you miss your period 2 months in a row, call your healthcare provider because you might be pregnant.3.You could become pregnant if you have sex in the 7 days after you restart your pills. You MUST use a non-hormonal birth control method (such as condoms or spermicide) as a back-up for those 7 days.

If you forget any of the 7 white “reminder” pills in Week 4:

Throw away the pills you missed. Keep taking 1 pill each day until the pack is empty. You do not need a back-up non-hormonal birth control method if you start your next pack on time.

FINALLY, IF YOU ARE STILL NOT SURE WHAT TO DO ABOUT THE PILLS YOU HAVE MISSED

Use a back-up non-hormonal birth control method anytime you have sex.

Keep taking one pill each day until you can reach your healthcare provider.

To report SUSPECTED ADVERSE REACTIONS, contact Northstar Rx LLC.Toll-free at 1-800-206-7821 or FDA at 1-800-FDA-1088 or www.fda.gov/medwatch.

Manufactured for: Northstar Rx LLC

Memphis TN 38141
Manufactured by: Novast Laboratories Ltd.
Nantong, China 226009

I0103 Rev. 01/2023 Rev. B

PACKAGE LABEL

Add image transcription here...